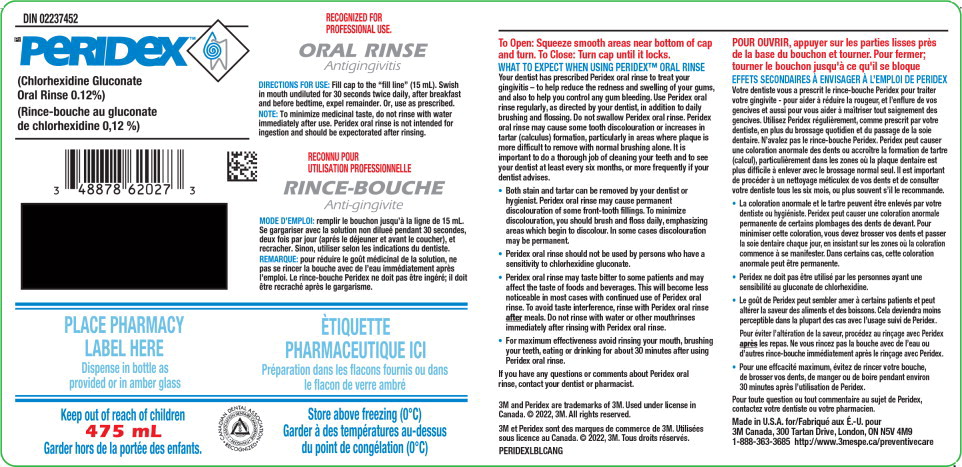 DRUG LABEL: Peridex
NDC: 48878-0620 | Form: RINSE
Manufacturer: Solventum US LLC
Category: otc | Type: HUMAN OTC DRUG LABEL
Date: 20240801

ACTIVE INGREDIENTS: Chlorhexidine Gluconate 1.2 mg/1 mL
INACTIVE INGREDIENTS: Glycerin; Saccharin Sodium; FD&C BLUE NO. 1; Water; Alcohol

RECOGNIZED FOR
PROFESSIONAL USE.
ORAL RINSE
Antigingivitis

DIRECTIONS FOR USE:

Fill cap to the “fill line” (15 mL). Swish in mouth undiluted for 30 seconds twice daily, after breakfast and before bedtime, expel remainder. Or, use as prescribed.

NOTE: To minimize medicinal taste, do not rinse with water immediately after use. Peridex is not intended for ingestion and should be expectorated after rinsing.

RECONNU POUR

UTILISATION PROFESSIONNELLE

RINCE-BOUCHE

Anti-gingivite

MODE D'EMPLOI:

remplir le bouchon jusqu'à la ligne de 15 mL. Se gargariser avec la solution non dilueé pendant 30 secondes, deux fois par jour (aprés le déjeuner et avant le coucher), et recracher. Sinon, utilizer selon les indications du dentiste.

REMARQUE: pour réduire le goût médicinal de la solution, ne pas se rincer la bouche avec de l'eau immédiatement après l'emploi. Le rince-bouche Peridex ne doit pas être ingéré; il doit être recraché après le gargarisme.

PLACE PHARMACY

LABEL HERE

Dispense in bottle as

provided or in amber glass

ÈTIQUETTE

PHARMACEUTIQUE ICI

Préparation dans les flacons fournis ou

dans le flacon de verre ambré

Keep out of reach of children

475 mL

Garder hors de la portée des enfants.

Store above freezing (0°C)

Garder à des températures au-dessus

Du point de congélation (0°C)

To Open: Squeeze smooth areas near bottom of cap and turn. To Close: Turn cap until it locks.

WHAT TO EXPECT WHEN USING PERIDEX™ ORAL RINSE

Your dentist has prescribed Peridex oral rinse to treat your gingivitis – to help reduce the redness and swelling of your gums, and also to help you control any gum bleeding. Use Peridex oral rinse regularly, as directed by your dentist, in addition to daily brushing and flossing. Do not swallow Peridex oral rinse. Peridex oral rinse may cause some tooth discolouration or increases in tartar (calculus) formation, particularly in areas where plaque is more difficult to remove with normal brushing alone. It is important to do a thorough job of cleaning your teeth and to see your dentist at least every six months, or more frequently if your dentist advises.

- Both stain and tartar can be removed by your dentist or hygienist. Peridex oral rinse may cause permanent discolouration of some front-tooth fillings. To minimize discolouration, you should brush and floss daily, emphasizing areas which begin to discolour. In some cases discolouration may be permanent.
- Peridex oral rinse should not be used by persons who have a sensitivity to chlorhexidine gluconate.
- Peridex oral rinse may taste bitter to some patients and may affect the taste of foods and beverages. This will become less noticeable in most cases with continued use of Peridex oral rinse. To avoid taste interference, rinse with Peridex oral rinse after meals. Do not rinse with water or other mouthrinses immediately after rinsing with Peridex oral rinse.
- For maximum effectiveness avoid rinsing your mouth, brushing your teeth, eating or drinking for about 30 minutes after using Peridex oral rinse.

If you have any questions or comments about Peridex oral

rinse, contact your dentist or pharmacist.

3M and Peridex are trademarks of 3M. Used under license in Canada. © 2022, 3M. All rights reserved.

3M et Peridex sont des marques de commerce de 3M. Utilisées sous licence au Canada. © 2022, 3M. Tous droits réservés.

PERIDEXLBLCANG

POUR OUVRIR, appuyer sur les parties lisses près de la base du bouchon et tourner. Pour fermer; tourner le bouchon jusqu'à ce qu'il se bloque

EFFETS SECONDAIRES À ENVISAGER À L'EMPLOI DE PERIDEX

Votre dentiste vous a prescrit le rince-bouche Peridex pour traiter votre gingivite - pour aider à réduire la rougeur, et l'enflure de vos gencives et aussi pour vous aider à maîtriser tout saignement des gencives. Utilisez Peridex régulièrement, comme prescrit par votre dentiste, en plus du brossage quotidien et du passage de la soie dentaire. N'avalez pas le rince-bouche Peridex. Peridex peut causer une coloration anormale des dents ou accroître la formation de tartre (calcul), particulièrement dans les zones où la plaque dentaire est plus difficile à enlever avec le brossage normal seul. Il est important de procéder à un nettoyage méticulex de vos dents et de consulter votre dentiste tous les six mois, ou plus souvent s'il le recommande.

- La coloration anormale et le tartre peuvent être enlevés par votre dentiste ou hygiéniste. Peridex peut causer une coloration anormale permanente de certains plombages des dents de devant. Pour minimiser cette coloration, vous devez brosser vos dents et passer la soie dentaire chaque jour, en insistant sur les zones où la coloration commence à se manifester. Dans certains cas, cette coloration anormale peut être permanente.
- Peridex ne doit pas être utilisé par les personnes ayant une sensibilité au gluconate de chlorhexidine.
- Le goût de Peridex peut sembler amer à certains patients et peut altérer la saveur des aliments et des boissons. Cela deviendra moins perceptible dans la plupart des cas avec l'usage suivi de Peridex. Pour éviter l'altération de la saveur, procédez au rinçage avec Peridex après les repas. Ne vous rincez pas la bouche avec de l'eau ou d'autres rince-bouche immédiatement après le rinçage avec Peridex.
- Pour une effcacité maximum, évitez de rincer votre bouche, de brosser vos dents, de manger ou de boire pendant environ 30 minutes après l'utilisation de Peridex.

Pour toute question ou tout commentaire au sujet de Peridex, contactez votre dentiste ou votre pharmacien.

Made in U.S.A. for/Fabriqué aux É.-U. pour

3M Canada, 300 Tartan Drive, London, ON N5V 4M9

1-888-363-3685 http://www.3mespe.ca/preventivecare

Principal Display Panel – 475 mL Label

DIN 02237452

Pr PERIDEX™

(Chlorhexidine Gluconate Oral Rinse 0.12%)

(Rince-bouche au gluconate de chlorhexidine 0,12 %)